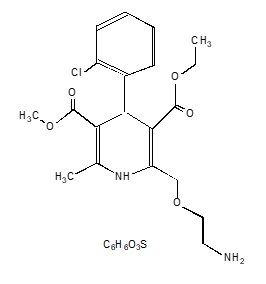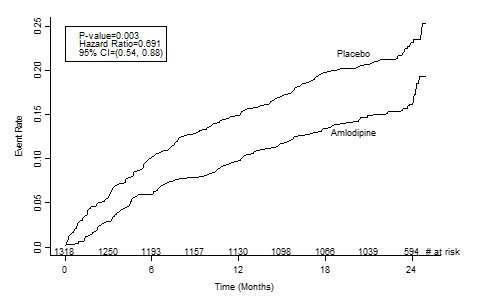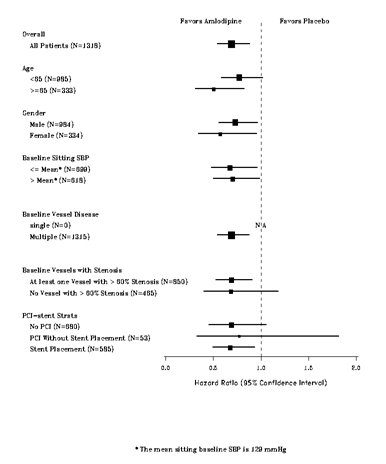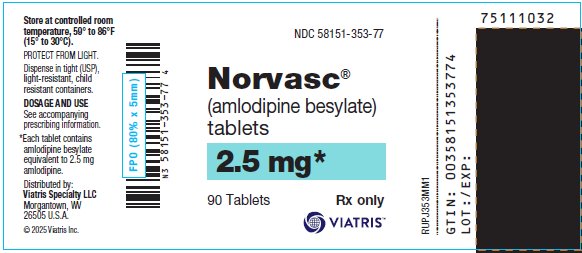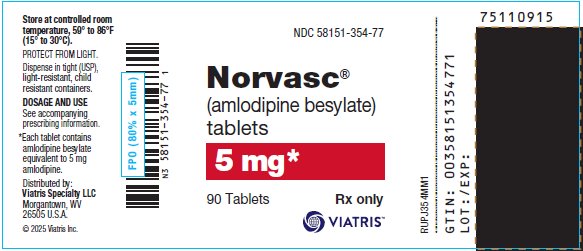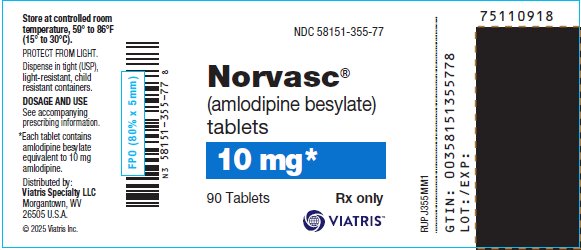 DRUG LABEL: Norvasc
NDC: 58151-353 | Form: TABLET
Manufacturer: Viatris Specialty LLC
Category: prescription | Type: HUMAN PRESCRIPTION DRUG LABEL
Date: 20230215

ACTIVE INGREDIENTS: AMLODIPINE BESYLATE 2.5 mg/1 1
INACTIVE INGREDIENTS: MICROCRYSTALLINE CELLULOSE; ANHYDROUS DIBASIC CALCIUM PHOSPHATE; SODIUM STARCH GLYCOLATE TYPE A POTATO; MAGNESIUM STEARATE

HIGHLIGHTS OF PRESCRIBING INFORMATION

These highlights do not include all the information needed to use NORVASC safely and effectively. See full prescribing information for NORVASC.
NORVASC® (amlodipine besylate) Tablets for oral administration
Initial U.S. Approval: 1992

1 INDICATIONS AND USAGE

NORVASC is a calcium channel blocker and may be used alone or in combination with other antihypertensive and antianginal agents for the treatment of:

- Hypertension (1.1)
  - NORVASC is indicated for the treatment of hypertension, to lower blood pressure. Lowering blood pressure reduces the risk of fatal and nonfatal cardiovascular events, primarily strokes and myocardial infarctions.
- Coronary Artery Disease (1.2)
  - Chronic Stable Angina
  - Vasospastic Angina (Prinzmetal’s or Variant Angina)
  - Angiographically Documented Coronary Artery Disease in patients without heart failure or an ejection fraction < 40%

2 DOSAGE AND ADMINISTRATION

- Adult recommended starting dose: 5 mg once daily with maximum dose 10 mg once daily. (2.1)
  - Small, fragile, or elderly patients, or patients with hepatic insufficiency may be started on 2.5 mg once daily. (2.1)
- Pediatric starting dose: 2.5 mg to 5 mg once daily. (2.2)

Important Limitation: Doses in excess of 5 mg daily have not been studied in pediatric patients. (2.2)

3 DOSAGE FORMS AND STRENGTHS

- Tablets: 2.5 mg, 5 mg, and 10 mg (3)

4 CONTRAINDICATIONS

- Known sensitivity to amlodipine (4)

5 WARNINGS AND PRECAUTIONS

- Symptomatic hypotension is possible, particularly in patients with severe aortic stenosis. However, acute hypotension is unlikely. (5.1)
- Worsening angina and acute myocardial infarction can develop after starting or increasing the dose of NORVASC, particularly in patients with severe obstructive coronary artery disease. (5.2)
- Titrate slowly in patients with severe hepatic impairment. (5.3)

6 ADVERSE REACTIONS

Most common adverse reaction to amlodipine is edema which occurred in a dose related manner. Other adverse experiences not dose related but reported with an incidence >1.0% are fatigue, nausea, abdominal pain, and somnolence. (6)

To report SUSPECTED ADVERSE REACTIONS, contact Viatris at 1-877-446-3679 (1-877-4-INFO-RX) or FDA at 1-800-FDA-1088 or www.fda.gov/medwatch.

7 DRUG INTERACTIONS

- Do not exceed doses greater than 20 mg daily of simvastatin. (7.2)

8 USE IN SPECIFIC POPULATIONS

- Pediatric: Effect on patients less than 6 years old is not known. (8.4)
- Geriatric: Start dosing at the low end of the dose range. (8.5)

FULL PRESCRIBING INFORMATION

1 INDICATIONS AND USAGE

1.1 Hypertension

NORVASC® is indicated for the treatment of hypertension, to lower blood pressure. Lowering blood pressure reduces the risk of fatal and nonfatal cardiovascular events, primarily strokes and myocardial infarctions. These benefits have been seen in controlled trials of antihypertensive drugs from a wide variety of pharmacologic classes including NORVASC.

Control of high blood pressure should be part of comprehensive cardiovascular risk management, including, as appropriate, lipid control, diabetes management, antithrombotic therapy, smoking cessation, exercise, and limited sodium intake. Many patients will require more than one drug to achieve blood pressure goals. For specific advice on goals and management, see published guidelines, such as those of the National High Blood Pressure Education Program’s Joint National Committee on Prevention, Detection, Evaluation, and Treatment of High Blood Pressure (JNC).

Numerous antihypertensive drugs, from a variety of pharmacologic classes and with different mechanisms of action, have been shown in randomized controlled trials to reduce cardiovascular morbidity and mortality, and it can be concluded that it is blood pressure reduction, and not some other pharmacologic property of the drugs, that is largely responsible for those benefits. The largest and most consistent cardiovascular outcome benefit has been a reduction in the risk of stroke, but reductions in myocardial infarction and cardiovascular mortality also have been seen regularly.

Elevated systolic or diastolic pressure causes increased cardiovascular risk, and the absolute risk increase per mmHg is greater at higher blood pressures, so that even modest reductions of severe hypertension can provide substantial benefit. Relative risk reduction from blood pressure reduction is similar across populations with varying absolute risk, so the absolute benefit is greater in patients who are at higher risk independent of their hypertension (for example, patients with diabetes or hyperlipidemia), and such patients would be expected to benefit from more aggressive treatment to a lower blood pressure goal.

Some antihypertensive drugs have smaller blood pressure effects (as monotherapy) in black patients, and many antihypertensive drugs have additional approved indications and effects (e.g., on angina, heart failure, or diabetic kidney disease). These considerations may guide selection of therapy.

NORVASC may be used alone or in combination with other antihypertensive agents.

1.2 Coronary Artery Disease (CAD)

Chronic Stable Angina

NORVASC is indicated for the symptomatic treatment of chronic stable angina. NORVASC may be used alone or in combination with other antianginal agents.

Vasospastic Angina (Prinzmetal’s or Variant Angina)

NORVASC is indicated for the treatment of confirmed or suspected vasospastic angina. NORVASC may be used as monotherapy or in combination with other antianginal agents.

Angiographically Documented CAD

In patients with recently documented CAD by angiography and without heart failure or an ejection fraction <40%, NORVASC is indicated to reduce the risk of hospitalization for angina and to reduce the risk of a coronary revascularization procedure.

2 DOSAGE AND ADMINISTRATION

2.1 Adults

The usual initial antihypertensive oral dose of NORVASC is 5 mg once daily, and the maximum dose is 10 mg once daily.

Small, fragile, or elderly patients, or patients with hepatic insufficiency may be started on 2.5 mg once daily and this dose may be used when adding NORVASC to other antihypertensive therapy.

Adjust dosage according to blood pressure goals. In general, wait 7 to 14 days between titration steps. Titrate more rapidly, however, if clinically warranted, provided the patient is assessed frequently.

Angina: The recommended dose for chronic stable or vasospastic angina is 5–10 mg, with the lower dose suggested in the elderly and in patients with hepatic insufficiency. Most patients will require 10 mg for adequate effect.

Coronary artery disease: The recommended dose range for patients with coronary artery disease is 5–10 mg once daily. In clinical studies, the majority of patients required 10 mg [see Clinical Studies (14.4)].

2.2 Children

The effective antihypertensive oral dose in pediatric patients ages 6–17 years is 2.5 mg to 5 mg once daily. Doses in excess of 5 mg daily have not been studied in pediatric patients [see Clinical Pharmacology (12.4), Clinical Studies (14.1)].

3 DOSAGE FORMS AND STRENGTHS

Tablets: 2.5 mg white, diamond, flat-faced, beveled edged, with “NORVASC” on one side and “2.5” on the other

Tablets: 5 mg white, elongated octagon, flat-faced, beveled edged, engraved with both “NORVASC” and “5” on one side and plain on the other

Tablets: 10 mg white, round, flat-faced, beveled edged, engraved with both “NORVASC” and “10” on one side and plain on the other

4 CONTRAINDICATIONS

NORVASC is contraindicated in patients with known sensitivity to amlodipine.

5 WARNINGS AND PRECAUTIONS

5.1 Hypotension

Symptomatic hypotension is possible, particularly in patients with severe aortic stenosis. Because of the gradual onset of action, acute hypotension is unlikely.

5.2 Increased Angina or Myocardial Infarction

Worsening angina and acute myocardial infarction can develop after starting or increasing the dose of NORVASC, particularly in patients with severe obstructive coronary artery disease.

5.3 Patients with Hepatic Failure

Because NORVASC is extensively metabolized by the liver and the plasma elimination half‑life (t 1/2) is 56 hours in patients with impaired hepatic function, titrate slowly when administering NORVASC to patients with severe hepatic impairment.

6 ADVERSE REACTIONS

6.1 Clinical Trials Experience

Because clinical trials are conducted under widely varying conditions, adverse reaction rates observed in the clinical trials of a drug cannot be directly compared to rates in the clinical trials of another drug and may not reflect the rates observed in practice.

NORVASC has been evaluated for safety in more than 11,000 patients in U.S. and foreign clinical trials. In general, treatment with NORVASC was well‑tolerated at doses up to 10 mg daily. Most adverse reactions reported during therapy with NORVASC were of mild or moderate severity. In controlled clinical trials directly comparing NORVASC (N=1730) at doses up to 10 mg to placebo (N=1250), discontinuation of NORVASC because of adverse reactions was required in only about 1.5% of patients and was not significantly different from placebo (about 1%). The most commonly reported side effects more frequent than placebo are reflected in the table below. The incidence (%) of side effects that occurred in a dose related manner are as follows:

 |  | Amlodipine |  | Placebo
 | 2.5 mg | 5 mg | 10 mg
 | N=275 | N=296 | N=268 | N=520
Edema | 1.8 | 3.0 | 10.8 | 0.6
Dizziness | 1.1 | 3.4 | 3.4 | 1.5
Flushing | 0.7 | 1.4 | 2.6 | 0.0
Palpitation | 0.7 | 1.4 | 4.5 | 0.6

Other adverse reactions that were not clearly dose related but were reported with an incidence greater than 1.0% in placebo‑controlled clinical trials include the following:

 | NORVASC (%) | Placebo (%)
 | (N=1730) | (N=1250)
Fatigue | 4.5 | 2.8
Nausea | 2.9 | 1.9
Abdominal Pain | 1.6 | 0.3
Somnolence | 1.4 | 0.6

For several adverse experiences that appear to be drug and dose related, there was a greater incidence in women than men associated with amlodipine treatment as shown in the following table:

 | NORVASC |  | Placebo
 | Male=% | Female=% | Male=% | Female=%
 | (N=1218) | (N=512) | (N=914) | (N=336)
Edema | 5.6 | 14.6 | 1.4 | 5.1
Flushing | 1.5 | 4.5 | 0.3 | 0.9
Palpitations | 1.4 | 3.3 | 0.9 | 0.9
Somnolence | 1.3 | 1.6 | 0.8 | 0.3

The following events occurred in <1% but >0.1% of patients in controlled clinical trials or under conditions of open trials or marketing experience where a causal relationship is uncertain; they are listed to alert the physician to a possible relationship:

Cardiovascular: arrhythmia (including ventricular tachycardia and atrial fibrillation), bradycardia, chest pain, peripheral ischemia, syncope, tachycardia, vasculitis.

Central and Peripheral Nervous System: hypoesthesia, neuropathy peripheral, paresthesia, tremor, vertigo.

Gastrointestinal: anorexia, constipation, dysphagia, diarrhea, flatulence, pancreatitis, vomiting, gingival hyperplasia.

General: allergic reaction, asthenia,^1 back pain, hot flushes, malaise, pain, rigors, weight gain, weight decrease.

Musculoskeletal System: arthralgia, arthrosis, muscle cramps,^1 myalgia.

Psychiatric: sexual dysfunction (male^1 and female), insomnia, nervousness, depression, abnormal dreams, anxiety, depersonalization.

Respiratory System: dyspnea,^1 epistaxis.

Skin and Appendages: angioedema, erythema multiforme, pruritus,^1 rash,^1 rash erythematous, rash maculopapular.

Special Senses: abnormal vision, conjunctivitis, diplopia, eye pain, tinnitus.

Urinary System: micturition frequency, micturition disorder, nocturia.

Autonomic Nervous System: dry mouth, sweating increased.

Metabolic and Nutritional: hyperglycemia, thirst.

Hemopoietic: leukopenia, purpura, thrombocytopenia.

^1 These events occurred in less than 1% in placebo‑controlled trials, but the incidence of these side effects was between 1% and 2% in all multiple dose studies.

NORVASC therapy has not been associated with clinically significant changes in routine laboratory tests. No clinically relevant changes were noted in serum potassium, serum glucose, total triglycerides, total cholesterol, HDL cholesterol, uric acid, blood urea nitrogen, or creatinine.

In the CAMELOT and PREVENT studies [see Clinical Studies (14.4)], the adverse event profile was similar to that reported previously (see above), with the most common adverse event being peripheral edema.

6.2 Postmarketing Experience

Because these reactions are reported voluntarily from a population of uncertain size, it is not always possible to reliably estimate their frequency or establish a causal relationship to drug exposure.

The following postmarketing event has been reported infrequently where a causal relationship is uncertain: gynecomastia. In postmarketing experience, jaundice and hepatic enzyme elevations (mostly consistent with cholestasis or hepatitis), in some cases severe enough to require hospitalization, have been reported in association with use of amlodipine.

Postmarketing reporting has also revealed a possible association between extrapyramidal disorder and amlodipine.

NORVASC has been used safely in patients with chronic obstructive pulmonary disease, well‑compensated congestive heart failure, coronary artery disease, peripheral vascular disease, diabetes mellitus, and abnormal lipid profiles.

7 DRUG INTERACTIONS

7.1 Impact of Other Drugs on Amlodipine

CYP3A Inhibitors

Co-administration with CYP3A inhibitors (moderate and strong) results in increased systemic exposure to amlodipine and may require dose reduction. Monitor for symptoms of hypotension and edema when amlodipine is co-administered with CYP3A inhibitors to determine the need for dose adjustment [see Clinical Pharmacology (12.3)].

CYP3A Inducers

No information is available on the quantitative effects of CYP3A inducers on amlodipine. Blood pressure should be closely monitored when amlodipine is co-administered with CYP3A inducers.

Sildenafil

Monitor for hypotension when sildenafil is co-administered with amlodipine [see Clinical Pharmacology (12.2)].

7.2 Impact of Amlodipine on Other Drugs

Simvastatin

Co-administration of simvastatin with amlodipine increases the systemic exposure of simvastatin. Limit the dose of simvastatin in patients on amlodipine to 20 mg daily [see Clinical Pharmacology (12.3)].

Immunosuppressants

Amlodipine may increase the systemic exposure of cyclosporine or tacrolimus when co-administered. Frequent monitoring of trough blood levels of cyclosporine and tacrolimus is recommended and adjust the dose when appropriate [see Clinical Pharmacology (12.3)].

8 USE IN SPECIFIC POPULATIONS

8.1 Pregnancy

Risk Summary

The limited available data based on post-marketing reports with NORVASC use in pregnant women are not sufficient to inform a drug-associated risk for major birth defects and miscarriage. There are risks to the mother and fetus associated with poorly controlled hypertension in pregnancy [see Clinical Considerations]. In animal reproduction studies, there was no evidence of adverse developmental effects when pregnant rats and rabbits were treated orally with amlodipine maleate during organogenesis at doses approximately 10 and 20-times the maximum recommended human dose (MRHD), respectively. However for rats, litter size was significantly decreased (by about 50%) and the number of intrauterine deaths was significantly increased (about 5-fold). Amlodipine has been shown to prolong both the gestation period and the duration of labor in rats at this dose [see Data].

The estimated background risk of major birth defects and miscarriage for the indicated population is unknown. All pregnancies have a background risk of birth defect, loss or other adverse outcomes. In the U.S. general population, the estimated background risk of major birth defects and miscarriage in clinically recognized pregnancies is 2%-4% and 15%‑20%, respectively.

Clinical Considerations

Disease-associated maternal and/or embryo/fetal risk

Hypertension in pregnancy increases the maternal risk for pre-eclampsia, gestational diabetes, premature delivery, and delivery complications (e.g., need for cesarean section and post-partum hemorrhage). Hypertension increases the fetal risk for intrauterine growth restriction and intrauterine death. Pregnant women with hypertension should be carefully monitored and managed accordingly.

Data

Animal Data

No evidence of teratogenicity or other embryo/fetal toxicity was found when pregnant rats and rabbits were treated orally with amlodipine maleate at doses up to 10 mg amlodipine/kg/day (approximately 10 and 20 times the MRHD based on body surface area, respectively) during their respective periods of major organogenesis. However for rats, litter size was significantly decreased (by about 50%) and the number of intrauterine deaths was significantly increased (about 5‑fold) in rats receiving amlodipine maleate at a dose equivalent to 10 mg amlodipine/kg/day for 14 days before mating and throughout mating and gestation. Amlodipine maleate has been shown to prolong both the gestation period and the duration of labor in rats at this dose.

8.2 Lactation

Risk Summary

Limited available data from a published clinical lactation study reports that amlodipine is present in human milk at an estimated median relative infant dose of 4.2%. No adverse effects of amlodipine on the breastfed infant have been observed. There is no available information on the effects of amlodipine on milk production.

8.4 Pediatric Use

NORVASC (2.5 to 5 mg daily) is effective in lowering blood pressure in patients 6 to 17 years [see Clinical Studies (14.1)].
Effect of NORVASC on blood pressure in patients less than 6 years of age is not known.

8.5 Geriatric Use

Clinical studies of NORVASC did not include sufficient numbers of subjects aged 65 and over to determine whether they respond differently from younger subjects. Other reported clinical experience has not identified differences in responses between the elderly and younger patients. In general, dose selection for an elderly patient should be cautious, usually starting at the low end of the dosing range, reflecting the greater frequency of decreased hepatic, renal, or cardiac function, and of concomitant disease or other drug therapy. Elderly patients have decreased clearance of amlodipine with a resulting increase of AUC of approximately 40–60%, and a lower initial dose may be required [see Dosage and Administration (2.1)].

10 OVERDOSAGE

Overdosage might be expected to cause excessive peripheral vasodilation with marked hypotension and possibly a reflex tachycardia. In humans, experience with intentional overdosage of NORVASC is limited.

Single oral doses of amlodipine maleate equivalent to 40 mg amlodipine/kg and 100 mg amlodipine/kg in mice and rats, respectively, caused deaths. Single oral amlodipine maleate doses equivalent to 4 or more mg amlodipine/kg or higher in dogs (11 or more times the maximum recommended human dose on a mg/m^2 basis) caused a marked peripheral vasodilation and hypotension.

If massive overdose should occur, initiate active cardiac and respiratory monitoring. Frequent blood pressure measurements are essential. Should hypotension occur, provide cardiovascular support including elevation of the extremities and the judicious administration of fluids. If hypotension remains unresponsive to these conservative measures, consider administration of vasopressors (such as phenylephrine) with attention to circulating volume and urine output. As NORVASC is highly protein bound, hemodialysis is not likely to be of benefit.

11 DESCRIPTION

NORVASC is the besylate salt of amlodipine, a long‑acting calcium channel blocker.

Amlodipine besylate is chemically described as 3-Ethyl-5-methyl (±)-2-[(2-aminoethoxy)methyl]-4‑(2‑chlorophenyl)‑1,4‑dihydro‑6‑methyl‑3,5‑pyridinedicarboxylate, monobenzenesulphonate. Its empirical formula is C20H25CIN2O5•C6H6O3S, and its structural formula is:

Amlodipine besylate is a white crystalline powder with a molecular weight of 567.1. It is slightly soluble in water and sparingly soluble in ethanol. NORVASC (amlodipine besylate) Tablets are formulated as white tablets equivalent to 2.5, 5, and 10 mg of amlodipine for oral administration. In addition to the active ingredient, amlodipine besylate, each tablet contains the following inactive ingredients: microcrystalline cellulose, dibasic calcium phosphate anhydrous, sodium starch glycolate, and magnesium stearate.

12 CLINICAL PHARMACOLOGY

12.1 Mechanism of Action

Amlodipine is a dihydropyridine calcium antagonist (calcium ion antagonist or slow‑channel blocker) that inhibits the transmembrane influx of calcium ions into vascular smooth muscle and cardiac muscle. Experimental data suggest that amlodipine binds to both dihydropyridine and nondihydropyridine binding sites. The contractile processes of cardiac muscle and vascular smooth muscle are dependent upon the movement of extracellular calcium ions into these cells through specific ion channels. Amlodipine inhibits calcium ion influx across cell membranes selectively, with a greater effect on vascular smooth muscle cells than on cardiac muscle cells. Negative inotropic effects can be detected in vitro but such effects have not been seen in intact animals at therapeutic doses. Serum calcium concentration is not affected by amlodipine. Within the physiologic pH range, amlodipine is an ionized compound (pKa=8.6), and its kinetic interaction with the calcium channel receptor is characterized by a gradual rate of association and dissociation with the receptor binding site, resulting in a gradual onset of effect.

Amlodipine is a peripheral arterial vasodilator that acts directly on vascular smooth muscle to cause a reduction in peripheral vascular resistance and reduction in blood pressure.

The precise mechanisms by which amlodipine relieves angina have not been fully delineated, but are thought to include the following:

Exertional Angina: In patients with exertional angina, NORVASC reduces the total peripheral resistance (afterload) against which the heart works and reduces the rate pressure product, and thus myocardial oxygen demand, at any given level of exercise.

Vasospastic Angina: NORVASC has been demonstrated to block constriction and restore blood flow in coronary arteries and arterioles in response to calcium, potassium epinephrine, serotonin, and thromboxane A2 analog in experimental animal models and in human coronary vessels in vitro. This inhibition of coronary spasm is responsible for the effectiveness of NORVASC in vasospastic (Prinzmetal’s or variant) angina.

12.2 Pharmacodynamics

Hemodynamics: Following administration of therapeutic doses to patients with hypertension, NORVASC produces vasodilation resulting in a reduction of supine and standing blood pressures. These decreases in blood pressure are not accompanied by a significant change in heart rate or plasma catecholamine levels with chronic dosing. Although the acute intravenous administration of amlodipine decreases arterial blood pressure and increases heart rate in hemodynamic studies of patients with chronic stable angina, chronic oral administration of amlodipine in clinical trials did not lead to clinically significant changes in heart rate or blood pressures in normotensive patients with angina.

With chronic once daily oral administration, antihypertensive effectiveness is maintained for at least 24 hours. Plasma concentrations correlate with effect in both young and elderly patients. The magnitude of reduction in blood pressure with NORVASC is also correlated with the height of pretreatment elevation; thus, individuals with moderate hypertension (diastolic pressure 105–114 mmHg) had about a 50% greater response than patients with mild hypertension (diastolic pressure 90–104 mmHg). Normotensive subjects experienced no clinically significant change in blood pressures

(+1/–2 mmHg).

In hypertensive patients with normal renal function, therapeutic doses of NORVASC resulted in a decrease in renal vascular resistance and an increase in glomerular filtration rate and effective renal plasma flow without change in filtration fraction or proteinuria.

As with other calcium channel blockers, hemodynamic measurements of cardiac function at rest and during exercise (or pacing) in patients with normal ventricular function treated with NORVASC have generally demonstrated a small increase in cardiac index without significant influence on dP/dt or on left ventricular end diastolic pressure or volume. In hemodynamic studies, NORVASC has not been associated with a negative inotropic effect when administered in the therapeutic dose range to intact animals and man, even when co‑administered with beta‑blockers to man. Similar findings, however, have been observed in normal or well‑compensated patients with heart failure with agents possessing significant negative inotropic effects.

Electrophysiologic Effects: NORVASC does not change sinoatrial nodal function or atrioventricular conduction in intact animals or man. In patients with chronic stable angina, intravenous administration of 10 mg did not significantly alter A‑H and H‑V conduction and sinus node recovery time after pacing. Similar results were obtained in patients receiving NORVASC and concomitant beta-blockers. In clinical studies in which NORVASC was administered in combination with beta‑blockers to patients with either hypertension or angina, no adverse effects on electrocardiographic parameters were observed. In clinical trials with angina patients alone, NORVASC therapy did not alter electrocardiographic intervals or produce higher degrees of AV blocks.

Drug interactions

Sildenafil

When amlodipine and sildenafil were used in combination, each agent independently exerted its own blood pressure lowering effect [see Drug Interactions (7.1)].

12.3 Pharmacokinetics

After oral administration of therapeutic doses of NORVASC, absorption produces peak plasma concentrations between 6 and 12 hours. Absolute bioavailability has been estimated to be between 64 and 90%. The bioavailability of NORVASC is not altered by the presence of food.

Amlodipine is extensively (about 90%) converted to inactive metabolites via hepatic metabolism with 10% of the parent compound and 60% of the metabolites excreted in the urine. Ex vivo studies have shown that approximately 93% of the circulating drug is bound to plasma proteins in hypertensive patients. Elimination from the plasma is biphasic with a terminal elimination half‑life of about 30–50 hours. Steady‑state plasma levels of amlodipine are reached after 7 to 8 days of consecutive daily dosing.

The pharmacokinetics of amlodipine are not significantly influenced by renal impairment. Patients with renal failure may therefore receive the usual initial dose.

Elderly patients and patients with hepatic insufficiency have decreased clearance of amlodipine with a resulting increase in AUC of approximately 40–60%, and a lower initial dose may be required. A similar increase in AUC was observed in patients with moderate to severe heart failure.

Drug interactions

In vitro data indicate that amlodipine has no effect on the human plasma protein binding of digoxin, phenytoin, warfarin, and indomethacin.

Impact of other drugs on amlodipine

Co-administered cimetidine, magnesium-and aluminum hydroxide antacids, sildenafil, and grapefruit juice have no impact on the exposure to amlodipine.

CYP3A inhibitors: Co-administration of a 180 mg daily dose of diltiazem with 5 mg amlodipine in elderly hypertensive patients resulted in a 60% increase in amlodipine systemic exposure. Erythromycin co-administration in healthy volunteers did not significantly change amlodipine systemic exposure. However, strong inhibitors of CYP3A (e.g., itraconazole, clarithromycin) may increase the plasma concentrations of amlodipine to a greater extent [see Drug Interactions (7.1)].

Impact of amlodipine on other drugs

Amlodipine is a weak inhibitor of CYP3A and may increase exposure to CYP3A substrates.

Co-administered amlodipine does not affect the exposure to atorvastatin, digoxin, ethanol and the warfarin prothrombin response time.

Simvastatin: Co-administration of multiple doses of 10 mg of amlodipine with 80 mg simvastatin resulted in a 77% increase in exposure to simvastatin compared to simvastatin alone [see Drug Interactions (7.2)].

Cyclosporine: A prospective study in renal transplant patients (N=11) showed on an average of 40% increase in trough cyclosporine levels when concomitantly treated with amlodipine [see Drug Interactions (7.2)].

Tacrolimus: A prospective study in healthy Chinese volunteers (N=9) with CYP3A5 expressers showed a 2.5- to 4-fold increase in tacrolimus exposure when concomitantly administered with amlodipine compared to tacrolimus alone. This finding was not observed in CYP3A5 non-expressers (N= 6). However, a 3-fold increase in plasma exposure to tacrolimus in a renal transplant patient (CYP3A5 non-expresser) upon initiation of amlodipine for the treatment of post-transplant hypertension resulting in reduction of tacrolimus dose has been reported. Irrespective of the CYP3A5 genotype status, the possibility of an interaction cannot be excluded with these drugs [see Drug Interactions (7.2)].

12.4 Pediatric Patients

Sixty-two hypertensive patients aged 6 to 17 years received doses of NORVASC between 1.25 mg and 20 mg. Weight-adjusted clearance and volume of distribution were similar to values in adults.

13 NONCLINICAL TOXICOLOGY

13.1 Carcinogenesis, Mutagenesis, Impairment of Fertility

Rats and mice treated with amlodipine maleate in the diet for up to two years, at concentrations calculated to provide daily dosage levels of 0.5, 1.25, and 2.5 amlodipine mg/kg/day, showed no evidence of a carcinogenic effect of the drug. For the mouse, the highest dose was, on a mg/m^2 basis, similar to the maximum recommended human dose of 10 mg amlodipine/day.^3 For the rat, the highest dose was, on a mg/m^2 basis, about twice the maximum recommended human dose.^3

Mutagenicity studies conducted with amlodipine maleate revealed no drug related effects at either the gene or chromosome level.

There was no effect on the fertility of rats treated orally with amlodipine maleate (males for 64 days and females for 14 days prior to mating) at doses up to 10 mg amlodipine/kg/day (8 times the maximum recommended human dose^3 of 10 mg/day on a mg/m^2 basis).

^3 Based on patient weight of 50 kg

14 CLINICAL STUDIES

14.1 Effects in Hypertension

Adult Patients

The antihypertensive efficacy of NORVASC has been demonstrated in a total of 15 double‑blind, placebo‑controlled, randomized studies involving 800 patients on NORVASC and 538 on placebo. Once daily administration produced statistically significant placebo‑corrected reductions in supine and standing blood pressures at 24 hours postdose, averaging about 12/6 mmHg in the standing position and 13/7 mmHg in the supine position in patients with mild to moderate hypertension. Maintenance of the blood pressure effect over the 24‑hour dosing interval was observed, with little difference in peak and trough effect. Tolerance was not demonstrated in patients studied for up to 1 year. The 3 parallel, fixed dose, dose response studies showed that the reduction in supine and standing blood pressures was dose‑related within the recommended dosing range. Effects on diastolic pressure were similar in young and older patients. The effect on systolic pressure was greater in older patients, perhaps because of greater baseline systolic pressure. Effects were similar in black patients and in white patients.

Pediatric Patients

Two hundred sixty-eight hypertensive patients aged 6 to 17 years were randomized first to NORVASC 2.5 or 5 mg once daily for 4 weeks and then randomized again to the same dose or to placebo for another 4 weeks. Patients receiving 2.5 mg or 5 mg at the end of 8 weeks had significantly lower systolic blood pressure than those secondarily randomized to placebo. The magnitude of the treatment effect is difficult to interpret, but it is probably less than 5 mmHg systolic on the 5 mg dose and 3.3 mmHg systolic on the 2.5 mg dose. Adverse events were similar to those seen in adults.

14.2 Effects in Chronic Stable Angina

The effectiveness of 5–10 mg/day of NORVASC in exercise‑induced angina has been evaluated in 8 placebo‑controlled, double‑blind clinical trials of up to 6 weeks duration involving 1038 patients (684 NORVASC, 354 placebo) with chronic stable angina. In 5 of the 8 studies, significant increases in exercise time (bicycle or treadmill) were seen with the 10 mg dose. Increases in symptom‑limited exercise time averaged 12.8% (63 sec) for NORVASC 10 mg, and averaged 7.9% (38 sec) for NORVASC 5 mg. NORVASC 10 mg also increased time to 1 mm ST segment deviation in several studies and decreased angina attack rate. The sustained efficacy of NORVASC in angina patients has been demonstrated over long‑term dosing. In patients with angina, there were no clinically significant reductions in blood pressures (4/1 mmHg) or changes in heart rate (+0.3 bpm).

14.3 Effects in Vasospastic Angina

In a double‑blind, placebo‑controlled clinical trial of 4 weeks duration in 50 patients, NORVASC therapy decreased attacks by approximately 4/week compared with a placebo decrease of approximately 1/week (p<0.01). Two of 23 NORVASC and 7 of 27 placebo patients discontinued from the study due to lack of clinical improvement.

14.4 Effects in Documented Coronary Artery Disease

In PREVENT, 825 patients with angiographically documented coronary artery disease were randomized to NORVASC

(5–10 mg once daily) or placebo and followed for 3 years. Although the study did not show significance on the primary objective of change in coronary luminal diameter as assessed by quantitative coronary angiography, the data suggested a favorable outcome with respect to fewer hospitalizations for angina and revascularization procedures in patients with CAD.

CAMELOT enrolled 1318 patients with CAD recently documented by angiography, without left main coronary disease and without heart failure or an ejection fraction <40%. Patients (76% males, 89% Caucasian, 93% enrolled at US sites, 89% with a history of angina, 52% without PCI, 4% with PCI and no stent, and 44% with a stent) were randomized to double-blind treatment with either NORVASC (5–10 mg once daily) or placebo in addition to standard care that included aspirin (89%), statins (83%), beta-blockers (74%), nitroglycerin (50%), anti-coagulants (40%), and diuretics (32%), but excluded other calcium channel blockers. The mean duration of follow-up was 19 months. The primary endpoint was the time to first occurrence of one of the following events: hospitalization for angina pectoris, coronary revascularization, myocardial infarction, cardiovascular death, resuscitated cardiac arrest, hospitalization for heart failure, stroke/TIA, or peripheral vascular disease. A total of 110 (16.6%) and 151 (23.1%) first events occurred in the NORVASC and placebo groups, respectively, for a hazard ratio of 0.691 (95% CI: 0.540–0.884, p = 0.003). The primary endpoint is summarized in Figure 1 below. The outcome of this study was largely derived from the prevention of hospitalizations for angina and the prevention of revascularization procedures (see Table 1). Effects in various subgroups are shown in Figure 2.

In an angiographic substudy (n=274) conducted within CAMELOT, there was no significant difference between amlodipine and placebo on the change of atheroma volume in the coronary artery as assessed by intravascular ultrasound.

Figure 1 - Kaplan-Meier Analysis of Composite Clinical Outcomes for NORVASC versus Placebo
Figure 2 – Effects on Primary Endpoint of NORVASC versus Placebo across Sub-Groups

Table 1 below summarizes the significant composite endpoint and clinical outcomes from the composites of the primary endpoint. The other components of the primary endpoint including cardiovascular death, resuscitated cardiac arrest, myocardial infarction, hospitalization for heart failure, stroke/TIA, or peripheral vascular disease did not demonstrate a significant difference between NORVASC and placebo.

Table 1. Incidence of Significant Clinical Outcomes for CAMELOT
Clinical Outcomes N (%) | NORVASC (N=663) | Placebo (N=655) | Risk Reduction (p-value)
Composite CV Endpoint | 110 (16.6) | 151 (23.1) | 31% (0.003)
Hospitalization for Angina [Total patients with these events] | 51 (7.7) | 84 (12.8) | 42% (0.002)
Coronary Revascularization | 78 (11.8) | 103 (15.7) | 27% (0.033)

14.5 Studies in Patients with Heart Failure

NORVASC has been compared to placebo in four 8–12 week studies of patients with NYHA Class II/III heart failure, involving a total of 697 patients. In these studies, there was no evidence of worsened heart failure based on measures of exercise tolerance, NYHA classification, symptoms, or left ventricular ejection fraction. In a long‑term (follow‑up at least 6 months, mean 13.8 months) placebo‑controlled mortality/morbidity study of NORVASC 5–10 mg in 1153 patients with NYHA Classes III (n=931) or IV (n=222) heart failure on stable doses of diuretics, digoxin, and ACE inhibitors, NORVASC had no effect on the primary endpoint of the study which was the combined endpoint of all‑cause mortality and cardiac morbidity (as defined by life‑threatening arrhythmia, acute myocardial infarction, or hospitalization for worsened heart failure), or on NYHA classification, or symptoms of heart failure. Total combined all‑cause mortality and cardiac morbidity events were 222/571 (39%) for patients on NORVASC and 246/583 (42%) for patients on placebo; the cardiac morbid events represented about 25% of the endpoints in the study.

Another study (PRAISE-2) randomized patients with NYHA Class III (80%) or IV (20%) heart failure without clinical symptoms or objective evidence of underlying ischemic disease, on stable doses of ACE inhibitors (99%), digitalis (99%), and diuretics (99%), to placebo (n=827) or NORVASC (n=827) and followed them for a mean of 33 months. There was no statistically significant difference between NORVASC and placebo in the primary endpoint of all-cause mortality (95% confidence limits from 8% reduction to 29% increase on NORVASC). With NORVASC there were more reports of pulmonary edema.

16 HOW SUPPLIED/STORAGE AND HANDLING

2.5 mg Tablets

NORVASC – 2.5 mg Tablets (amlodipine besylate equivalent to 2.5 mg of amlodipine per tablet) are supplied as white, diamond, flat‑faced, beveled edged engraved with “NORVASC” on one side and “2.5” on the other side and supplied as follows:

NDC 58151-353-77 Bottle of 90

5 mg Tablets

NORVASC – 5 mg Tablets (amlodipine besylate equivalent to 5 mg of amlodipine per tablet) are white, elongated octagon, flat‑faced, beveled edged engraved with both “NORVASC” and “5” on one side and plain on the other side and supplied as follows:

NDC 58151-354-77 Bottle of 90
NDC 58151-354-88 Unit Dose package of 100
NDC 58151-354-30 Bottle of 300

10 mg Tablets

NORVASC – 10 mg Tablets (amlodipine besylate equivalent to 10 mg of amlodipine per tablet) are white, round, flat‑faced, beveled edged engraved with both “NORVASC” and “10” on one side and plain on the other side and supplied as follows:

NDC 58151-355-77 Bottle of 90
NDC 58151-355-88 Unit Dose package of 100

Storage

Store bottles at controlled room temperature, 59° to 86°F (15° to 30°C) and dispense in tight, light‑resistant containers (USP).

Distributed by:
Viatris Specialty LLC
Morgantown, WV 26505 U.S.A.

© 2023 Viatris Inc.

NORVASC is a registered trademark of Viatris Specialty LLC, a Viatris Company.

UPJ:NRVSCT:R1p

Revised: 2/2023

Patient Information

NORVASC®
(amlodipine besylate)
2.5 mg, 5 mg, and 10 mg tablets

Read this information carefully before you start taking NORVASC (NORE-vask) and each time you refill your prescription. There may be new information. This information does not replace talking with your doctor. If you have any questions about NORVASC, ask your doctor. Your doctor will know if NORVASC is right for you.

What is NORVASC?

NORVASC is a type of medicine known as a calcium channel blocker (CCB). It is used to treat high blood pressure (hypertension) and a type of chest pain called angina. It can be used by itself or with other medicines to treat these conditions.

High Blood Pressure (hypertension)

High blood pressure comes from blood pushing too hard against your blood vessels. NORVASC relaxes your blood vessels, which lets your blood flow more easily and helps lower your blood pressure. Drugs that lower blood pressure lower your risk of having a stroke or heart attack.

Angina

Angina is a pain or discomfort that keeps coming back when part of your heart does not get enough blood. Angina feels like a pressing or squeezing pain, usually in your chest under the breastbone. Sometimes you can feel it in your shoulders, arms, neck, jaws, or back. NORVASC can relieve this pain.

Who should not use NORVASC?

Do not use NORVASC if you are allergic to amlodipine (the active ingredient in NORVASC), or to the inactive ingredients. Your doctor or pharmacist can give you a list of these ingredients.

What should I tell my doctor before taking NORVASC?

Tell your doctor about any prescription and non-prescription medicines you are taking, including natural or herbal remedies.

Tell your doctor if you:

- ever had heart disease
- ever had liver problems
- are pregnant, or plan to become pregnant. Your doctor will decide if NORVASC is the best treatment for you.
- are breast-feeding. NORVASC passes into your milk.

How should I take NORVASC?

- Take NORVASC once a day, with or without food.
- It may be easier to take your dose if you do it at the same time every day, such as with breakfast or dinner, or at bedtime. Do not take more than one dose of NORVASC at a time.
- If you miss a dose, take it as soon as you remember. Do not take NORVASC if it has been more than 12 hours since you missed your last dose. Wait and take the next dose at your regular time.
- Other medicines: You can use nitroglycerin and NORVASC together. If you take nitroglycerin for angina, don’t stop taking it while you are taking NORVASC.
- While you are taking NORVASC, do not stop taking your other prescription medicines, including any other blood pressure medicines, without talking to your doctor.
- If you took too much NORVASC, call your doctor or Poison Control Center, or go to the nearest hospital emergency room right away.

What should I avoid while taking NORVASC?

- Do not start any new prescription or non-prescription medicines or supplements, unless you check with your doctor first.

What are the possible side effects of NORVASC?

NORVASC may cause the following side effects. Most side effects are mild or moderate:

- swelling of your legs or ankles
- tiredness, extreme sleepiness
- stomach pain, nausea
- dizziness
- flushing (hot or warm feeling in your face)
- arrhythmia (irregular heartbeat)
- heart palpitations (very fast heartbeat)
- muscle rigidity, tremor and/or abnormal muscle movement

It is rare, but when you first start taking NORVASC or increase your dose, you may have a heart attack or your angina may get worse. If that happens, call your doctor right away or go directly to a hospital emergency room.

Tell your doctor if you are concerned about any side effects you experience. These are not all the possible side effects of NORVASC. For a complete list, ask your doctor or pharmacist.

How do I store NORVASC?

Keep NORVASC away from children. Store NORVASC Tablets at room temperature (between 59° and 86°F). Keep NORVASC out of the light. Do not store in the bathroom. Keep NORVASC in a dry place.

General advice about NORVASC

Sometimes, doctors will prescribe a medicine for a condition that is not written in the patient information leaflets. Only use NORVASC the way your doctor told you to. Do not give NORVASC to other people, even if they have the same symptoms you have. It may harm them.

You can ask your pharmacist or doctor for information about NORVASC, or you can contact Viatris at 1-877-446-3679 (1-877-4-INFO-RX).

Distributed by:
Viatris Specialty LLC
Morgantown, WV 26505 U.S.A.

© 2023 Viatris Inc.

NORVASC is a registered trademark of Viatris Specialty LLC, a Viatris Company.

UPJ:PL:NRVSCT:R1p

Revised: 2/2023

PRINCIPAL DISPLAY PANEL – 2.5 mg Bottle

NDC 58151-353-77

Norvasc®
(amlodipine besylate)
tablets

2.5 mg *

90 Tablets

Rx only

Store at controlled room
temperature, 59° to 86°F
(15° to 30°C).

PROTECT FROM LIGHT.

Dispense in tight (USP),
light-resistant, child
resistant containers.

DOSAGE AND USE

See accompanying
prescribing information.

*Each tablet contains
amlodipine besylate
equivalent to 2.5 mg
amlodipine.

Distributed by:
Viatris Specialty LLC
Morgantown, WV

26505 U.S.A.

© 2025 Viatris Inc.

RUPJ353MM1

PRINCIPAL DISPLAY PANEL – 5 mg Bottle

NDC 58151-354-77

Norvasc®
(amlodipine besylate)
tablets

5 mg *

90 Tablets

Rx only

Store at controlled room
temperature, 59° to 86°F
(15° to 30°C).

PROTECT FROM LIGHT.

Dispense in tight (USP),
light-resistant, child
resistant containers.

DOSAGE AND USE

See accompanying
prescribing information.

*Each tablet contains
amlodipine besylate
equivalent to 5 mg
amlodipine.

Distributed by:
Viatris Specialty LLC
Morgantown, WV

26505 U.S.A.

© 2025 Viatris Inc.

RUPJ354MM1

PRINCIPAL DISPLAY PANEL - 10 mg Bottle

NDC 58151-355-77

Norvasc®
(amlodipine besylate)
tablets

10 mg *

90 Tablets

Rx only

Store at controlled room
temperature, 59° to 86°F
(15° to 30°C).

PROTECT FROM LIGHT.

Dispense in tight (USP),
light-resistant, child
resistant containers.

DOSAGE AND USE

See accompanying
prescribing information.

*Each tablet contains
amlodipine besylate
equivalent to 10 mg
amlodipine.

Distributed by:
Viatris Specialty LLC
Morgantown, WV

26505 U.S.A.

© 2025 Viatris Inc.

RUPJ355MM1